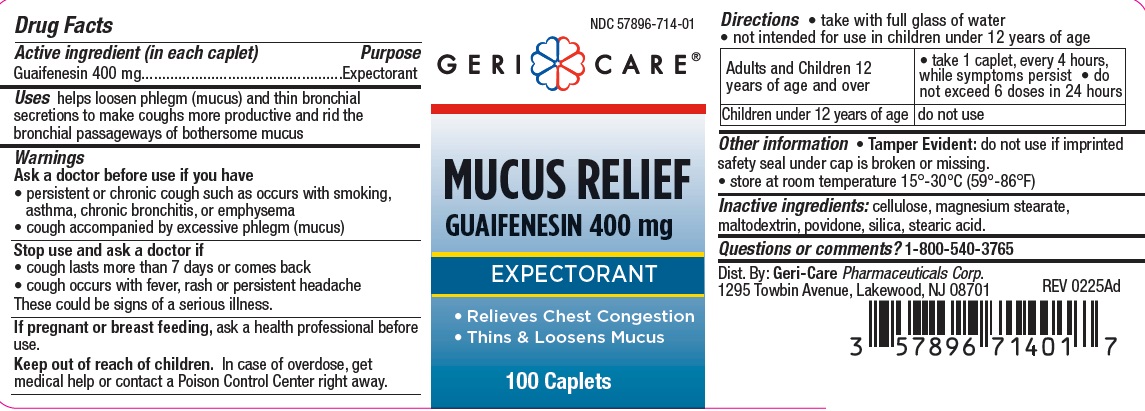 DRUG LABEL: MUCUS RELIEF
NDC: 57896-714 | Form: TABLET
Manufacturer: Geri-Care Pharmaceuticals, Corp
Category: otc | Type: HUMAN OTC DRUG LABEL
Date: 20251117

ACTIVE INGREDIENTS: GUAIFENESIN 400 mg/1 1
INACTIVE INGREDIENTS: CELLULOSE, MICROCRYSTALLINE; MAGNESIUM STEARATE; MALTODEXTRIN; POVIDONE; SILICON DIOXIDE; STEARIC ACID

gc 714

Active ingredient (in each caplet)

Guaifenesin 400 mg

Purpose

Expectorant

Uses

helps loosen phlegm (mucus) and thin bronchial secretions to make coughs more productive to rid the bronchial passageways
of bothersome mucus

Warnings

Ask a doctor before use if you have

- persistent or chronic cough such as occurs with smoking, asthma, chronic bronchitis, or emphysema
- cough accompanied by excessive phlegm (mucus)

Stop use and ask a doctor if

- cough lasts more than 7 days or comes back
- cough occurs with fever, rash or persistent headache
- these could be signs of a serious illness.

If pregnant or breast feeding, ask a health professional before use.

Keep out of reach of children. In case of overdose, get medical help or contact a Poison Control Center right away.

Directions

- take with full glass of water
- not intended for use in children under 12 years of age

adults and children 12 years of age and over | • take 1 caplet, every 4 hours, while symptoms persist • do not exceed 6 doses in 24 hours
children under 12 years of age | do not use

Other information

• Tamper Evident: do not use if imprinted safety seal under cap is broken or missing.

• store at room temperature 15°-30°C (59°-86°F)

Inactive ingredients

cellulose, magnesium stearate, maltodextrin, povidone, silica, stearic acid.

Questions or comments?

1-800-540-3765